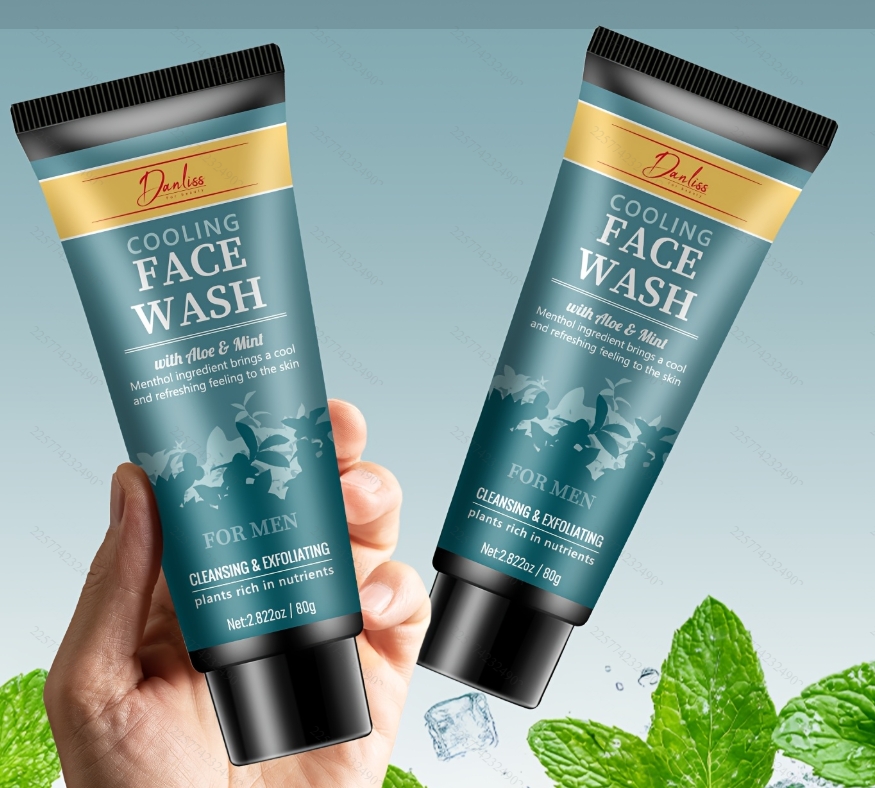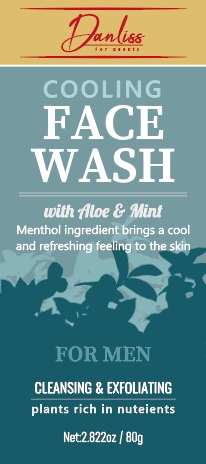 DRUG LABEL: Cooling Face Wash
NDC: 84025-282 | Form: CREAM
Manufacturer: Guangzhou Yanxi Biotechnology Co., Ltd
Category: otc | Type: HUMAN OTC DRUG LABEL
Date: 20241218

ACTIVE INGREDIENTS: SORBITOL 4 mg/80 g; NIACINAMIDE 3 mg/80 g
INACTIVE INGREDIENTS: WATER

DOSAGE AND ADMINISTRATION

Wet your face, apply the cleanser with your fingertips or a damp washcloth, and massage gently in a circular motion.Rinse throughly with wam water for a refreshing cleansing.

WARNINGS

Keep out of children

INACTIVE INGREDIENT

Aqua

INDICATIONS AND USAGE

For daily skin care

Keep out of children

PURPOSE

Skin clean